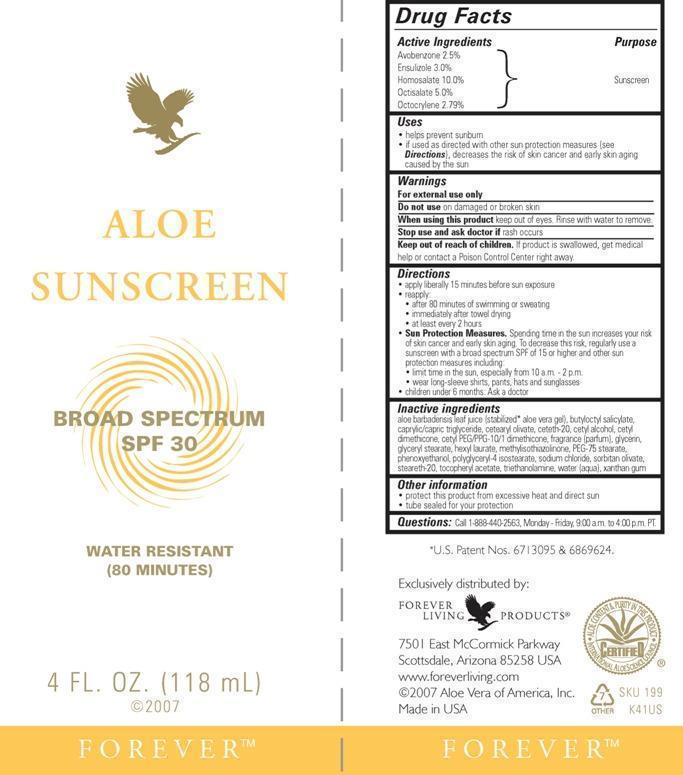 DRUG LABEL: Aloe Sunscreen
NDC: 11697-199 | Form: LOTION
Manufacturer: Aloe Vera of America, Inc.
Category: otc | Type: HUMAN OTC DRUG LABEL
Date: 20150121

ACTIVE INGREDIENTS: HOMOSALATE 10.0 g/100 mL; OCTISALATE 5.0 g/100 mL; AVOBENZONE 2.5 g/100 mL; ENSULIZOLE 3.0 g/100 mL; OCTOCRYLENE 2.79 g/100 mL
INACTIVE INGREDIENTS: ALOE VERA LEAF 29.4 g/100 mL; WATER 29.2 g/100 mL; BUTYLOCTYL SALICYLATE 3.0 g/100 mL; MEDIUM-CHAIN TRIGLYCERIDES 3.0 g/100 mL; GLYCERIN 2.0 g/100 mL; CETEARYL OLIVATE 1.7 g/100 mL; SORBITAN OLIVATE 1.4 g/100 mL; SODIUM CHLORIDE 1.0 g/100 mL; CETYL ALCOHOL 0.7 g/100 mL; GLYCERYL MONOSTEARATE 0.7 g/100 mL; POLYGLYCERYL-4 ISOSTEARATE 0.7 g/100 mL; HEXYL LAURATE 0.7 g/100 mL; PHENOXYETHANOL 0.3 g/100 mL; PEG-75 STEARATE 0.3 g/100 mL; TRIETHYLAMINE 0.3 g/100 mL; XANTHAN GUM 0.2 g/100 mL; CETETH-20 0.2 g/100 mL; STEARETH-20 0.1 g/100 mL; ALPHA-TOCOPHEROL ACETATE 0.1 g/100 mL; METHYLISOTHIAZOLINONE 0.01 g/100 mL

Active Ingredients Purpose

Avobenzone 2.5%

Ensulizole 3.0%

Homosalate 10.0%

Octisalate 5.0%

Octocrylene 2.79% Sunscreen

Uses

- helps prevent sunburn
- if used as directed with other sun protection measures (see Directions), decreases the risk of skin cancer and early skin aging caused by the sun

Warnings

For external use only

Do not use on damaged or broken skin

When using this product keep out of eyes. Rinse with water to remove.

Stop use and ask doctor if rash occurs

Keep out of reach of children. If product is swallowed, get medical help or contact a Poison Control Center right away.

Directions

- apply liberally 15 minutes before sun exposure
- rapply:
- after 80 minutes of swimming or sweating
- immediately after towel drying
- at least every 2 hours
- Sun Protection Measures. Spending time in the sun increases your risk of skin cancer and early skin aging. To decrease this risk, regularly use a sunscreen with a broad spectrum SPF of 15 or higher and other sun protection measures including:
- limit time in the sun, especially from 10 a.m. - 2 p.m.
- wear long-sleeve shirts, pants, hats and sunglasses
- children under 6 months: Ask a doctor

Inactive ingredients
aloe barbadensis leaf juice (stabilized* aloe vera gel), butyloctyl salicylate, caprylic/capric triglyceride, cetearyl olivate, ceteth-20, cetyl alcohol, cetyl dimethicone, cetyl PEG/PPG-10/1 dimethicone, fragrance (parfum), glycerin, glyceryl stearate, hexyl laurate, methylisothiazolinone, PEG-75 stearate, phenoxyethanol, polyglyceryl-4 isostearate, sodium chloride, sorbitan olivate, steareth-20, tocopheryl acetate, triethanolamine, water (aqua), xanthan gum

Other information

- protect this product from excessive heat and direct sun
- tube sealed for your protection

QUESTIONS

Questions: Call 1-888-440-2563, Monday - Friday, 9:00 a.m. to 4:00 p.m. PT.